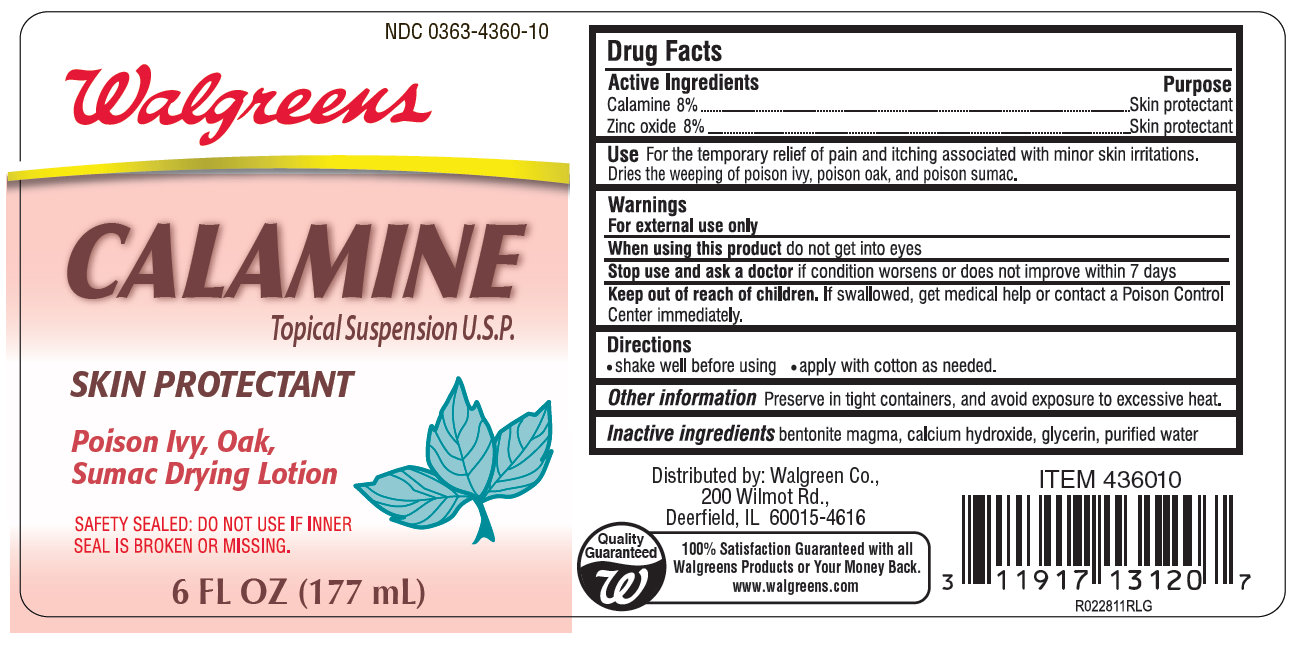 DRUG LABEL: Walgreens Calamine
NDC: 0363-4360 | Form: LOTION
Manufacturer: Walgreen Company
Category: otc | Type: HUMAN OTC DRUG LABEL
Date: 20111005

ACTIVE INGREDIENTS: FERRIC OXIDE RED 8 mL/100 mL; ZINC OXIDE 8 mL/100 mL
INACTIVE INGREDIENTS: BENTONITE; CALCIUM HYDROXIDE; GLYCERIN; WATER

Walgreens Calamine Topical Suspension U.S.P. Skin Protectant

Active Ingredients

Calamine 8%

Zinc oxide 8%

Purpose

Skin protectant

Use

For the temporary relief of pain and itching associated with minor skin irritations.

Dries the weeping of poison ivy, poison oak and poison sumac.

Warnings

For external use only

When using this product do not get into eyes

Stop use and ask a doctor if condition worsens or does not improve within 7 days

Keep out of reach of children. If swallowed, get medical help or contact a Poison Control Center immediately.

Directions

- shake well before using
- apply with cotton as needed

Other information

Preserve in tight containers, and avoid exposure to excessive heat.

Inactive ingredients

bentonite magma, calcium hydroxide, glycerin, purified water

Distributed by: Walgreen Co.,

200 Wilmot Rd.,

Deerfield, IL 60015-4616

Quality Guaranteed

100% Satisfaction Guaranteed with all Walgreens Products or Your Money Back.

www.walgreens.com

Front Panel Display Walgreens Calamine Topical Suspension U.S.P. Skin Protectant 177ml (0363-4360-10)

NDC 0363-4360-10
Walgreens
Calamine
Topical Suspension U.S.P.
Skin Protectant
Poison Ivy, Oak,
Sumac Dry Lotion
SAFETY SEALED: DO NOT USE IF INNER SEAL IS BROKEN OR MISSING
6 FL OZ (177 ml)